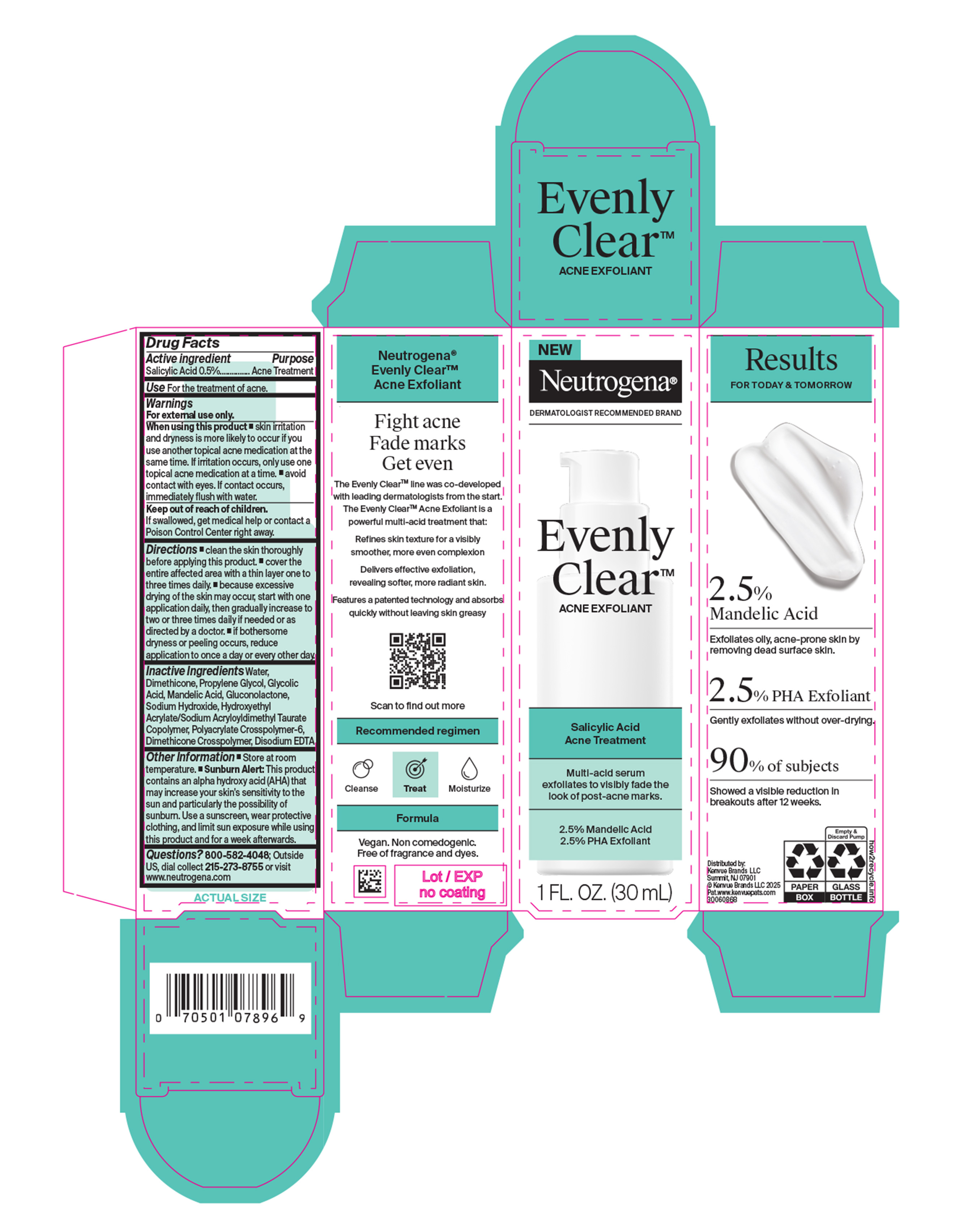 DRUG LABEL: Neutrogena Evenly Clear Acne Exfoliant
NDC: 69968-0944 | Form: LOTION
Manufacturer: Kenvue Brands LLC
Category: otc | Type: HUMAN OTC DRUG LABEL
Date: 20250926

ACTIVE INGREDIENTS: SALICYLIC ACID 5 mg/1 mL
INACTIVE INGREDIENTS: PROPYLENE GLYCOL; WATER; HYDROXYETHYL ACRYLATE/SODIUM ACRYLOYLDIMETHYL TAURATE COPOLYMER (100000 MPA.S AT 1.5%); EDETATE DISODIUM; POLYACRYLATE CROSSPOLYMER-6; DIMETHICONE CROSSPOLYMER; SODIUM HYDROXIDE; DIMETHICONE; GLYCOLIC ACID; GLUCONOLACTONE; MANDELIC ACID

Neutrogena Evenly Clear Acne Exfoliant

Drug Facts

Active Ingredient

Salicylic Acid 0.5%

Purpose

.Acne Treatment

Use

For the treatment of acne.

Warnings

For external use only.

When using this product

▪ skin irritation and dryness is more likely to occur if you use another topical acne medication at the same time. If irritation occurs, only use one topical acne medication at a time. ▪ avoid contact with eyes. If contact occurs, immediately flush with water.

Keep out of reach of children. If swallowed, get medical help or contact a Poison Control Center right away.

Directions

▪ clean the skin thoroughly before applying this product.

▪ cover the entire affected area with a thin layer one to three times daily.

▪ because excessive drying of the skin may occur, start with one application daily, then gradually increase to two or three times daily if needed or as directed by a doctor.

▪ if bothersome dryness or peeling occurs, reduce application to once a day or every other day.

Inactive Ingredients

Water, Dimethicone, Propylene Glycol, Glycolic Acid, Mandelic Acid, Gluconolactone, Sodium Hydroxide, Hydroxyethyl Acrylate/Sodium Acryloyldimethyl Taurate Copolymer, Polyacrylate Crosspolymer-6, Dimethicone Crosspolymer, Disodium EDTA

Other Information

- Store at Room Temperature. ▪ Sunburn Alert: This product contains an alpha hydroxy acid (AHA) that may increase your skin's sensitivity to the sun and particularly the possibility of sunburn. Use a sunscreen, wear protective clothing, and limit sun exposure while using this product and for a week afterwards.

Questions?

800-582-4048; Outside US, dial collect 215-273-8755 or visit www.neutrogena.com

Distributed by:

Kenvue Brands LLC

Summit, NJ 07901

PRINCIPAL DISPLAY PANEL - 30 mL Bottle in Carton Label

NEW

Neutrogena®

DERMATOLOGIST RECOMMENDED BRAND

Evenly

Clear™

ACNE EXFOLIANT

Salicylic Acid

Acne Treatment

Multi-acid serum

exfoliates to visibly fade the

look of post-acne marks.

2.5% Mandelic Acid

2.5% PHA Exfoliant

1 FL. OZ. (30 mL)